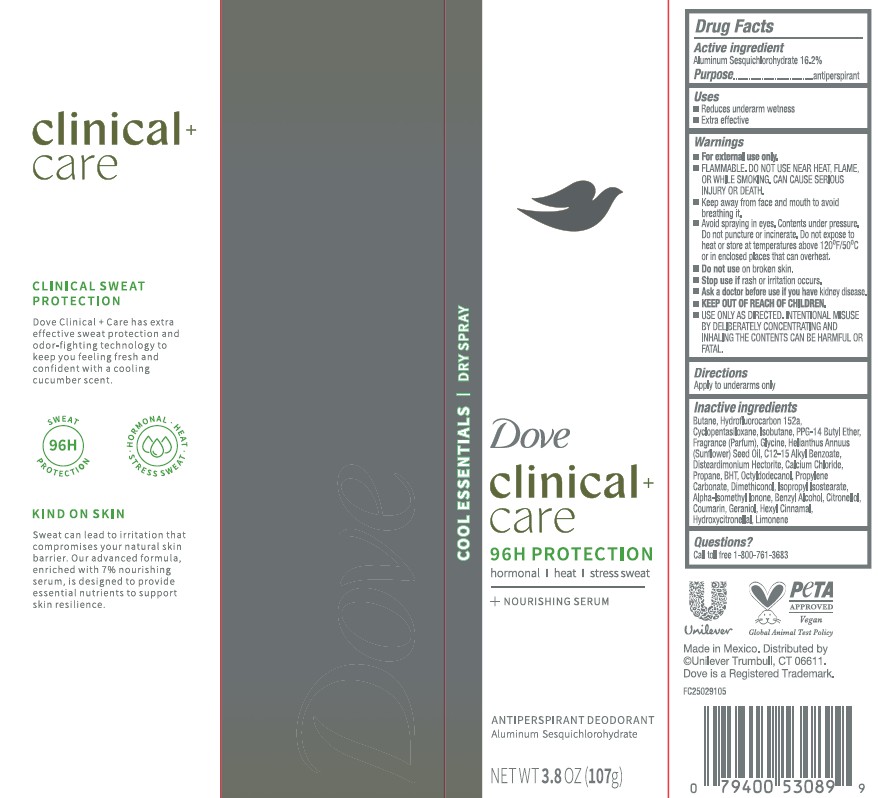 DRUG LABEL: Dove Clinical Care
NDC: 64942-2388 | Form: AEROSOL, SPRAY
Manufacturer: Conopco d/b/a Unilever
Category: otc | Type: HUMAN OTC DRUG LABEL
Date: 20251119

ACTIVE INGREDIENTS: ALUMINUM SESQUICHLOROHYDRATE 16.2 g/100 g
INACTIVE INGREDIENTS: HELIANTHUS ANNUUS (SUNFLOWER) SEED OIL; CITRONELLOL; CYCLOPENTASILOXANE; GLYCINE; ALPHA-ISOMETHYL IONONE; OCTYLDODECANOL; PROPYLENE CARBONATE; ISOPROPYL ISOSTEARATE; DISTEARDIMONIUM HECTORITE; BUTANE; PPG-14 BUTYL ETHER; C12-15 ALKYL BENZOATE; PROPANE; BHT; COUMARIN; GERANIOL; HYDROFLUOROCARBON 152A; ISOBUTANE; BENZYL ALCOHOL; LIMONENE, (+)-; CALCIUM CHLORIDE; DIMETHICONOL (40 CST); HEXYL CINNAMAL; HYDROXYCITRONELLOL

Dove Clinical + Care 96H Protection Cool Essentials Dry Spray Antiperspirant Deodorant

DESCRIPTION

Dove Clinical + Care 96H Protection Cool Essentials Dry Spray Antiperspirant Deodorant

ACTIVE INGREDIENT

Aluminum Sesquichlorohydrate 16.2%

PURPOSE

antiperspirant

INDICATIONS AND USAGE

reduces underarm wetness

extra effective

WARNINGS

• For external use only. • FLAMMABLE. DO NOT USE NEAR HEAT, FLAME, OR WHILE
SMOKING. CAN CAUSE SERIOUS INJURY OR DEATH. • Keep away from face and mouth to avoid breathing it.
• Avoid spraying in eyes. Contents under pressure. Do not puncture or incinerate. Do not expose to heat or
store at temperatures above 120ºF/50ºC or in enclosed places that can overheat. • Do not use on broken skin. • Stop use if rash or irritation occurs. • Ask a doctor before use if you have kidney disease. • USE ONLY AS DIRECTED. INTENTIONAL MISUSE BY DELIBERATELY CONCENTRATING AND INHALING THE CONTENTS CAN BE HARMFUL OR FATAL

• KEEP OUT OF REACH OF CHILDREN

DOSAGE AND ADMINISTRATION

apply to underarms only

INACTIVE INGREDIENT

Butane, Hydrofluorocarbon 152A, Cyclopentasiloxane, Isobutane, PPG-14 Butyl Ether, Glycine, Helianthus Annuus (Sunflower) Seed Oil, C12-15 Alkyl Benzoate, Disteardimonium Hectorite, Calcium Chloride, Propane, BHT, Octyldodecanol, Propylene Carbonate, Dimethiconol, Isopropyl Isostearate,Alpha-Isomethyl Ionone, Benzyl Alcohol, Citronellol, Coumarin, Geraniol, Hexyl Cinnamal, Hydroxycitronellol, Limonene

QUESTIONS

Call toll-free 1-800-761-3683